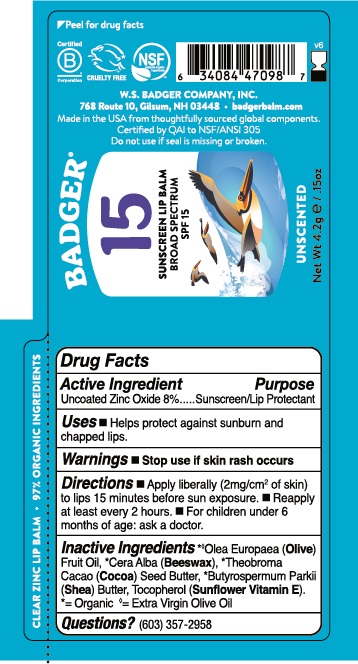 DRUG LABEL: Badger BROAD SPECTRUM SPF 15 Lip Balm
NDC: 62206-1542 | Form: STICK
Manufacturer: W.S. Badger Company, Inc.
Category: otc | Type: HUMAN OTC DRUG LABEL
Date: 20241231

ACTIVE INGREDIENTS: ZINC OXIDE 8 g/100 g
INACTIVE INGREDIENTS: OLIVE OIL; YELLOW WAX; COCOA BUTTER; SHEA BUTTER; TOCOPHEROL

Badger® BROAD SPECTRUM SPF 15 Lip Balm

Drug Facts

Active Ingredient

Non-Nano Uncoated Zinc Oxide 8%

Purpose

Sunscreen

Uses

- Helps prevent againt sunburn and chapped lips.

Warnings

Stop use if skin rash occurs

Keep out of reach of children.

Directions

■ Apply liberally (2mg/cm^2 of skin) to lips15 minutes before sun exposure

■ Reapply at least every 2 hours. ■ For children under 6 months of age: ask a doctor.

Ingredients

*◊ Olea Europaea (Olive) Fruit Oil, *Cera Alba (Beeswax), *Theobroma Cacao (Cocoa) Seed Butter, *Butyrospermum Parkii (Shea) Butter, Tocopherol (Sunflower Vitamin E).

Questions?

(603) 357-2958

PRINCIPAL DISPLAY PANEL

BADGER®

Broad Spectrum

SPF 15

LIP BALM

REEF FRIENDLY

CLEAR ZINC

NON GMO

NSF

WATER RESISTANT 40 Min

Gluten Free

CRUELTY FREE

Unscented

Net Wt 4.2g/.15 oz

97% Organic Ingredients